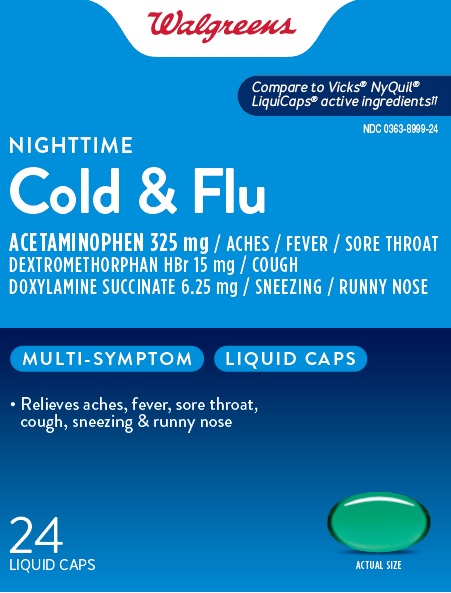 DRUG LABEL: Walgreens NightTime Cold and Flu
NDC: 0363-8999 | Form: CAPSULE, LIQUID FILLED
Manufacturer: WALGREEN COMPANY
Category: otc | Type: HUMAN OTC DRUG LABEL
Date: 20260119

ACTIVE INGREDIENTS: ACETAMINOPHEN 325 mg/1 1; DEXTROMETHORPHAN HYDROBROMIDE 15 mg/1 1; DOXYLAMINE SUCCINATE 6.25 mg/1 1
INACTIVE INGREDIENTS: D&C YELLOW NO. 10; FD&C BLUE NO. 1; GELATIN; GLYCERIN; POLYETHYLENE GLYCOL 400; POVIDONE K30; PROPYLENE GLYCOL; WATER; SORBITOL; SORBITAN; TITANIUM DIOXIDE

Walgreens NightTime Cold and Flu

Drug Facts

ACTIVE INGREDIENT

Active ingredients (in each softgel) | Purpose
Acetaminophen 325 mg | Pain reliever/fever reducer
Dextromethorphan Hydrobromide 15 mg | Cough suppressant
Doxylamine Succinate 6.25 mg | Antihistamine

Uses

temporarily relieves common cold/flu symptoms:

- cough due to minor throat and bronchial irritation
- sore throat
- headache
- minor aches/pains
- fever
- runny nose and sneezing

Warnings

Liver warning

This product contains acetaminophen. Severe liver damage may occur if you take:

- more than 4 doses in 24 hours, which is the maximum daily amount for this product.
- with other drugs containing acetaminophen
- 3 or more alcoholic drinks every day while using this product

Sore throat warning

If sore throat is severe, lasts for more than 2 days, or occurs with or is followed by fever, headache, rash, nausea, or vomiting, see a doctor promptly.

Do not use

- with any other drug containing acetaminophen (prescription or nonprescription). If you are not sure whether a drug contains acetaminophen, ask a doctor or pharmacist.
- If you are now taking a prescription monoamine oxidase inhibitor (MAOI) (certain drugs for depression, psychiatric or emotional conditions, or Parkinson's disease), or for 2 weeks after stopping the MAOI drug. If you do not know if your prescription drug contains an MAOI, ask a doctor or pharmacist before taking this product.
- to make a child sleep

Ask a doctor before use if you have

- liver disease
- glaucoma
- cough that occurs with too much phlegm (mucus)
- a breathing problem or chronic cough that lasts or as occurs with smoking, asthma, chronic bronchitis, or emphysema
- trouble urinating due to enlarged prostate gland

Ask a doctor or pharmacist before use if you are

- taking sedatives or tranquilizers
- taking the blood-thinning drug warfarin.

When using this product

- do not use more than directed
- excitability may occur especially in children
- marked drowsiness may occur
- avoid alcoholic drinks
- be careful with driving a motor vehicle or operating machinery
- alcohol, sedatives and tranquilizers may increase drowsiness

Stop use and ask a doctor if

- pain or cough gets worse or lasts more than 7 days
- fever gets worse or lasts more than 3 days
- redness or swelling is present
- new symptoms occur
- cough comes back or occurs with rash, or headache that lasts. These could be signs of a serious condition

PREGNANCY OR BREAST FEEDING

If pregnant or breast-feeding, ask a health professional before use.

Keep out of reach of children.

Overdose warning

Taking more than the recommended dose can cause serious health problems. In case of overdose, get medical help or contact a Poison Control Center right away. Quick medical attention is critical for adults as well as for children, even if you do not notice any signs or symptoms.

Directions

- Take only as recommended—see Overdose warning.
- do not exceed 4 doses per 24 hours
  adults and children 12 years of age and over | swallow 2 softgels with water every 6 hours
  children 4 to under 12 years of age | ask a doctor
  children under 4 years of age | do not use

When using other Daytime or Nighttime products, carefully read each label to ensure correct dosing

Other information

- store at room temperature 15°-30°C (59°-86°F) and avoid excessive heat

Inactive ingredients

D&C Yellow# 10, FD&C Blue# 1, gelatin, glycerin, polyethylene glycol, povidone, propylene glycol, purified water, sorbitol sorbitan, titanium dioxide

Questions or comments?

1-888-333-9792

PRINCIPAL DISPLAY PANEL

Walgreens

Cold & Flu

COMPARE TO ACTIVE INGREDIENTS IN
VICKS® NYQUIL® LiquiCaps® active ingredients††

MULTI-SYMPTOM

NIGHTTIME COLD & FLU

Acetaminophen 325mg/ ACHES/ FEVER/ SORE THROAT
Dextromethorphan HBr 15mg/ COUGH
Doxylamine Succinate 6.25mg/ SNEEZING/ RUNNY NOSE
Relieves aches, fever, sore throat,
cough, sneezing & runny nose

Actual Size

24 LIQUID CAPS

†††† This product is not manufactured or distributed by
Procter & Gamble, owner of the registered
trademarks Vicks® NyQuil® LiquiCaps®